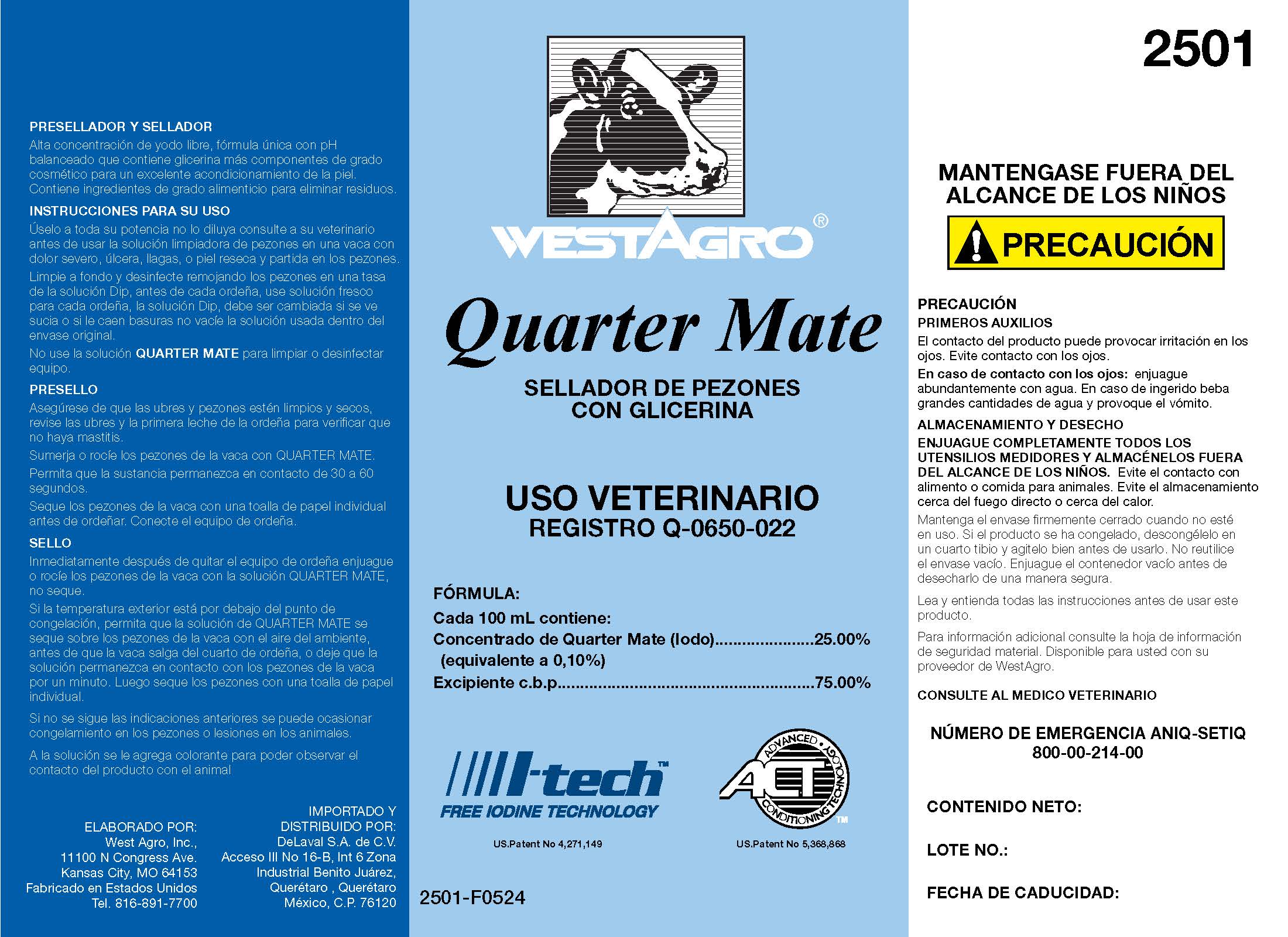 DRUG LABEL: Quarter Mate
NDC: 33392-501 | Form: SOLUTION
Manufacturer: WestAgro, Inc.
Category: animal | Type: OTC ANIMAL DRUG LABEL
Date: 20240514

ACTIVE INGREDIENTS: Iodine 1.0 g/1 L
INACTIVE INGREDIENTS: FD&C BLUE NO. 1; SODIUM HYDROXIDE; ANHYDROUS CITRIC ACID; POLOXAMER 335; GLYCERIN; XANTHAN GUM; POLYSORBATE 80; water; SODIUM CHLORIDE; FD&C RED NO. 40; FD&C YELLOW NO. 5; SODIUM IODIDE; DOCUSATE SODIUM; SODIUM IODATE

QUARTER MATE

PURPOSE

NIPPLE SEALANT WITH GLYCERINE

VETERINARY USE

REGISTRATION Q-0650-022

ACTIVE INGREDIENT

FORMULA:

Each 100 mL contains:

Quarter Mate Concentrate (Iodine)........................ 25.00%

(equivalent to 0.10%)

Excipient c.b.p................................................... 75.00%

PRESEALER AND SEALANT

High concentration of free iodine, unique pH balanced formula containing glycerin plus cosmetic grade components for excellent skin conditioning. Contains food grade ingredients to eliminate waste.

INDICATIONS AND USAGE

INSTRUCTIONS FOR USE

Use at full strength; do not dilute; please, consult your veterinarian before using teat cleansing solution on a cow with severe soreness, ulcer, sores, or dry, cracked skin on the teats. Clean thoroughly and disinfect by soaking the teats in a cup of Dip solution, before each milking, use fresh solution for each milking, the Dip solution should be changed if it looks dirty or if debris falls on it, do not empty the used solution inside from the original container.

Do not use QUARTER MATE solution to clean or disinfect the equipment.

PRESEAL

Make sure that the udders and teats are clean and dry, check the udders and the first milk from milking to verify that there is not mastitis.

Dip or spray the cow's teats with QUARTER MATE. Allow the substance to remain in contact for 30 to 60 seconds.

Dry the cow's teats with an individual paper tower before milking. Connect the milking equipment.

SEAL

Immediately after removing the milking equipment, rinse or spray the cow's teats with QUARTER MATE solution, do not blot.

If the outside temperature is below freezing, allow the QUARTER MATE solution to dry on the cow's teats with ambient air before the cow leaves the milking room, or allow the solution to remain in contact with the cow's teats for one minute. Then dry the nipples with an individual paper towel.

Failure to follow the above instructions may cause frostbite to the nipples or injuries to the animals.

Colorant is added to the solution to be able to observe the product contact with the animal.

KEEP OUT OF REACH OF CHILDREN

! CAUTION

GENERAL PRECAUTIONS

CAUTION

FIRST AID

Contact of the product may cause eye irritation. Avoid contact with eyes.

In case of contact with eyes: rinse thoroughly with water. If swallowed, drink large amounts of water and induce vomiting.

STORAGE AND DISPOSAL

COMPLETELY RINSE ALL MEASURING UTENSILS AND STORE THEM OUT OF REACH OF CHILDREN. Avoid contact with food or animal feed. Avoid storage near direct fire or near heat. Keep the container tightly closed when not in use. If the product has been frozen, thaw in a warm room and shake well before use. Do not reuse the empty container. Rinse the empty container before disposing of it safely.

GENERAL PRECAUTIONS

Read and understand all instructions before using this product.

For additional information, please consult the material safety information sheet. Available to you from your WestAgro supplier.

CONSULT YOUR VETERINARY DOCTOR

ANIQ-SETIQ EMERGENCY NUMBER 800-00-214-00

PACKAGE LABEL

Add image transcription here...